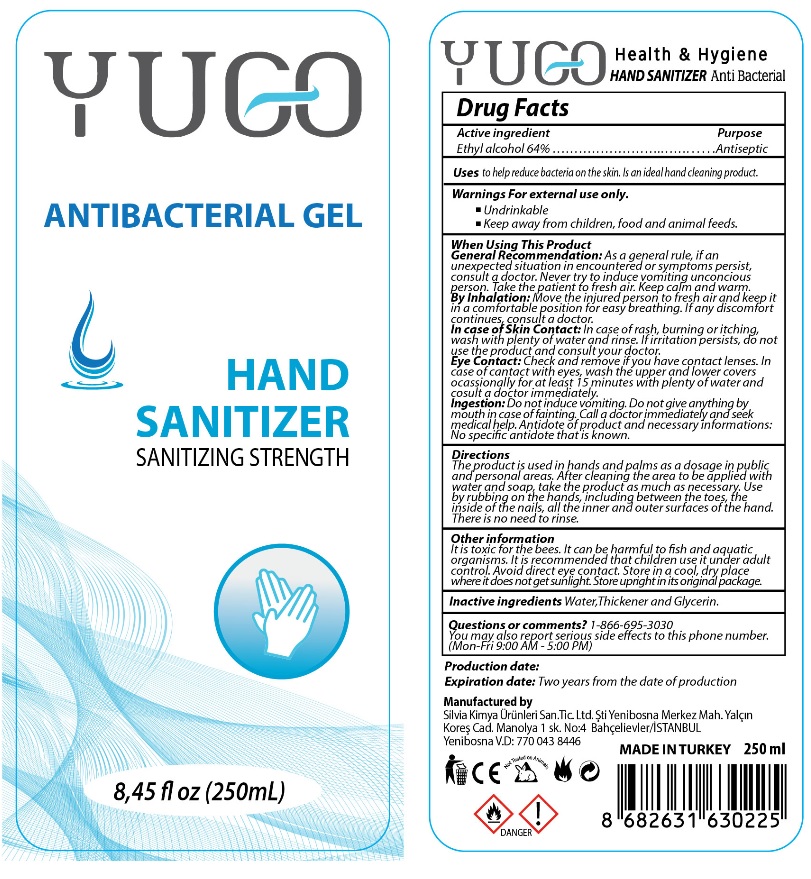 DRUG LABEL: YUGO
NDC: 79391-101 | Form: GEL
Manufacturer: SILVIA KIMYA URUNLERI SANAYI VE TICARET LIMITED SIRKETI
Category: otc | Type: HUMAN OTC DRUG LABEL
Date: 20200703

ACTIVE INGREDIENTS: ALCOHOL 64 mL/100 mL
INACTIVE INGREDIENTS: WATER; GLYCERIN

YUGO HAND SANITIZER

Active ingredient

Ethyl alcohol 64%

Purpose

Antiseptic

Uses

to help reduce bacteria on the skin. Is an ideal hand cleaning product.

Warnings For external use only.

- Undrinkable
- Keep away from children, food and animal feeds.

When Using This Product
General Recommendation: As a general rule, if an unexpected situation in encountered or symptoms persist, consult a doctor. Never try to induce vomiting unconscious person. Take the patient to fresh air. Keep calm and warm.
By Inhalation: Move the injured person to fresh air and keep it in a comfortable position for easy breathing. If any discomfort continues, consult a doctor.
In case of Skin Contact: In case of rash, burning or itching, wash with plenty of water and rinse. If irritation persists, do not use the product and consult your doctor.
Eye Contact: Check and remove if you have contact lenses. In case of contact with eyes, wash the upper and lower covers occasionally for at least 15 minutes with plenty of water and consult a doctor immediately.
Ingestion: Do not induce vomiting. Do not give anything by mouth in case of fainting. Call a doctor immediately and seek medical help. Antidote of product and necessary informations: No specific antidote that is known.

Keep out of reach of children.

Directions

The product is used in hands and palms as a dosage in public and personal areas. After cleaning the area to be applied with water and soap, take the product as much as necessary. Use by rubbing on the hands, including between the toes, the inside of the nails, all the inner and outer surfaces of the hand. There is no need to rinse.

Other information

It is toxic for the bees. It can be harmful to fish and aquatic organisms. It is recommended that children use it under adult control. Avoid direct eye contact. Store in a cool, dry place where it does not get sunlight. Store upright in its original package.

Inactive ingredients

Water, Thickener and Glycerin.

Questions or comments?

1-866-695-3030

You may also report serious side effects to this phone number.

(Mon-Fri 9:AM - 5:00 PM)

ANTIBACTERIAL GEL

SANITIZING STRENGTH

Production date:

Expiration date: Two years from the date of production

Manufactured by

Silvia Kimya Ürünleri San.Ve Tic.Ltd.Şti Yenibosna Merkez Mah. Yalçin Kores Cad. Maolya 1 sk. No:4 Bahçelievler/ISTANBUL

Yenibosna V.D: 770 043 8446

MADE IN TURKEY